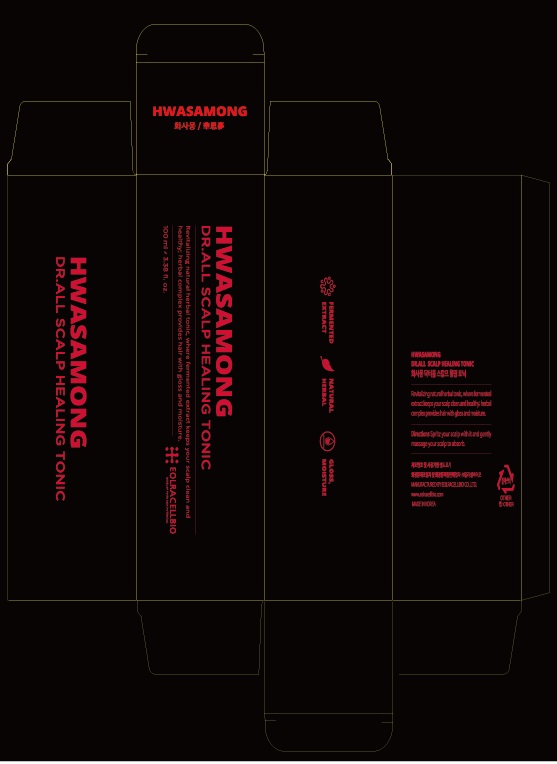 DRUG LABEL: HWASAMONG Dr.All Scalp Healing Tonic
NDC: 76678-0002 | Form: LIQUID
Manufacturer: Eolracellbio Co., Ltd.
Category: otc | Type: HUMAN OTC DRUG LABEL
Date: 20200510

ACTIVE INGREDIENTS: LONICERA JAPONICA FLOWER 10 g/100 mL; HOUTTUYNIA CORDATA WHOLE 7 g/100 mL
INACTIVE INGREDIENTS: BUTYLENE GLYCOL; 1,2-HEXANEDIOL

Drug Facts

ACTIVE INGREDIENT

Lonicera Japonica (Honeysuckle) Flower Extract, Houttuynia Cordata Extract

PURPOSE

hair protection, scalp clean, glossy hair, scalp nutrition

KEEP OUT OF REACH OF THE CHILDREN

WARNINGS

■ For external use only.

■ Do not use in eyes.

■ lf swallowed, get medical help promptly.

■ Stop use, ask doctor lf irritation occurs.

■ Keep out of reach of children.

DOSAGE AND ADMINISTRATION

for external use only

INACTIVE INGREDIENT

EcliptaProstrataExtract
CitrusUnshiuPeelExtract
MenthaArvensisExtract
PolygonumMultiflorumRootExtract
BiotaOrientalisLeafExtract
MorusAlbaLeafExtract
GlycineSoja(Soybean)SeedExtract
EckloniaCavaExtract
PerillaFrutescensLeafExtract
Camellia Sinensis Leaf Extract
Perilla Frutescens Leaf Extract
llicium Verum (Anise) Fruit Extract
Butylene Glycol
Caprylyl Glycol
1.2-Hexanediol

INDICATIONS AND USAGE

shake the tonic and spritz your scalp with it

gently massage your scalp to absorb